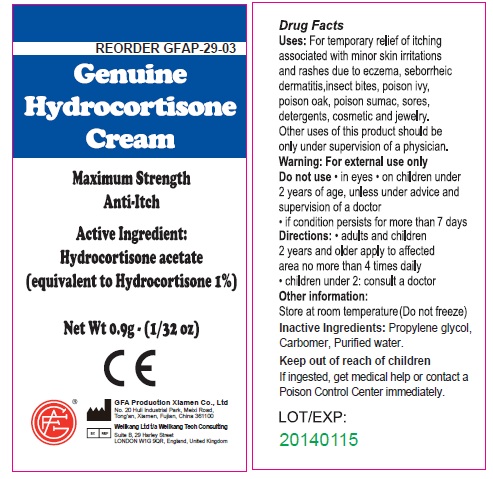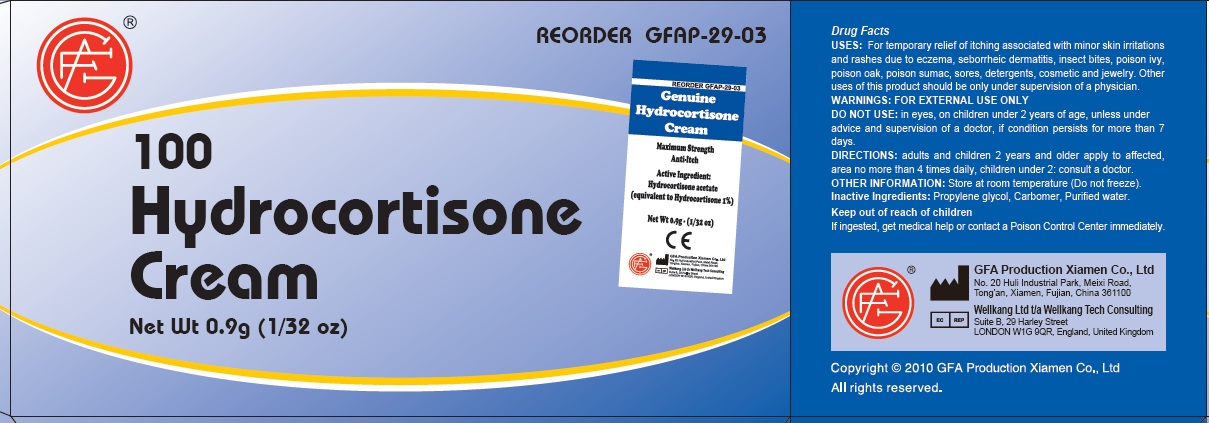 DRUG LABEL: Genuine Hydrocortisone
NDC: 52124-2903 | Form: CREAM
Manufacturer: Genuine First Aid, LLC
Category: otc | Type: HUMAN OTC DRUG LABEL
Date: 20110329

ACTIVE INGREDIENTS: HYDROCORTISONE ACETATE 1 g/100 g
INACTIVE INGREDIENTS: PROPYLENE GLYCOL; WATER

Genuine Hydrocortisone Cream

Active Ingredient

Hydrocortisone acetate (equivalent to Hydrocortisone 1%)

Purpose

Maximum strength Anti-itch

Uses

For temporary relief of itching associated with minor skin irritations and rashes due to eczema, seborrheic dermatitis, insect bites, poison ivy, poison oak, poison sumac, sores, detergents, cosmetic and jewelry. Other uses of this product should be only under supervision of a physician.

Warnings

For external use only

Do not use

in eyes, on children under 2 years of age, unless under advice and supervision of a doctor, if condition persists for more than 7 days.

Directions

adults and children 2 years and older apply to affected, area no more than 4 times daily, children under 2: consult a doctor.

Other Information

Store at room temperature (Do not freeze).

Inactive Ingredients

Propylene glycol, Carbomer, Purified water.

Keep out of reach of children

If ingested, get medical help or contact a Poison Control Center immediately.

GFA Production Xiamen Co., Ltd
No. 20 Huli Industrial Park, Meixi Road,
Tong'an, Xiamen, Fujian, China 361100

Wellkang Ltd t/a Wellkang Tech Consulting
Suite B, 29 Harley Street
LONDON W1G 9QR, England, United Kingdom

Copyright (c) 2010 GFA Production Xiamen Co., Ltd

All rights reserved

PACKAGE LABEL

Genuine Hydrocortisone Cream

Maximum Strength

Anti Itch

Active ingredient:

Hydrocortisone Acetate

(equivalent to Hydrocortisone 1%)